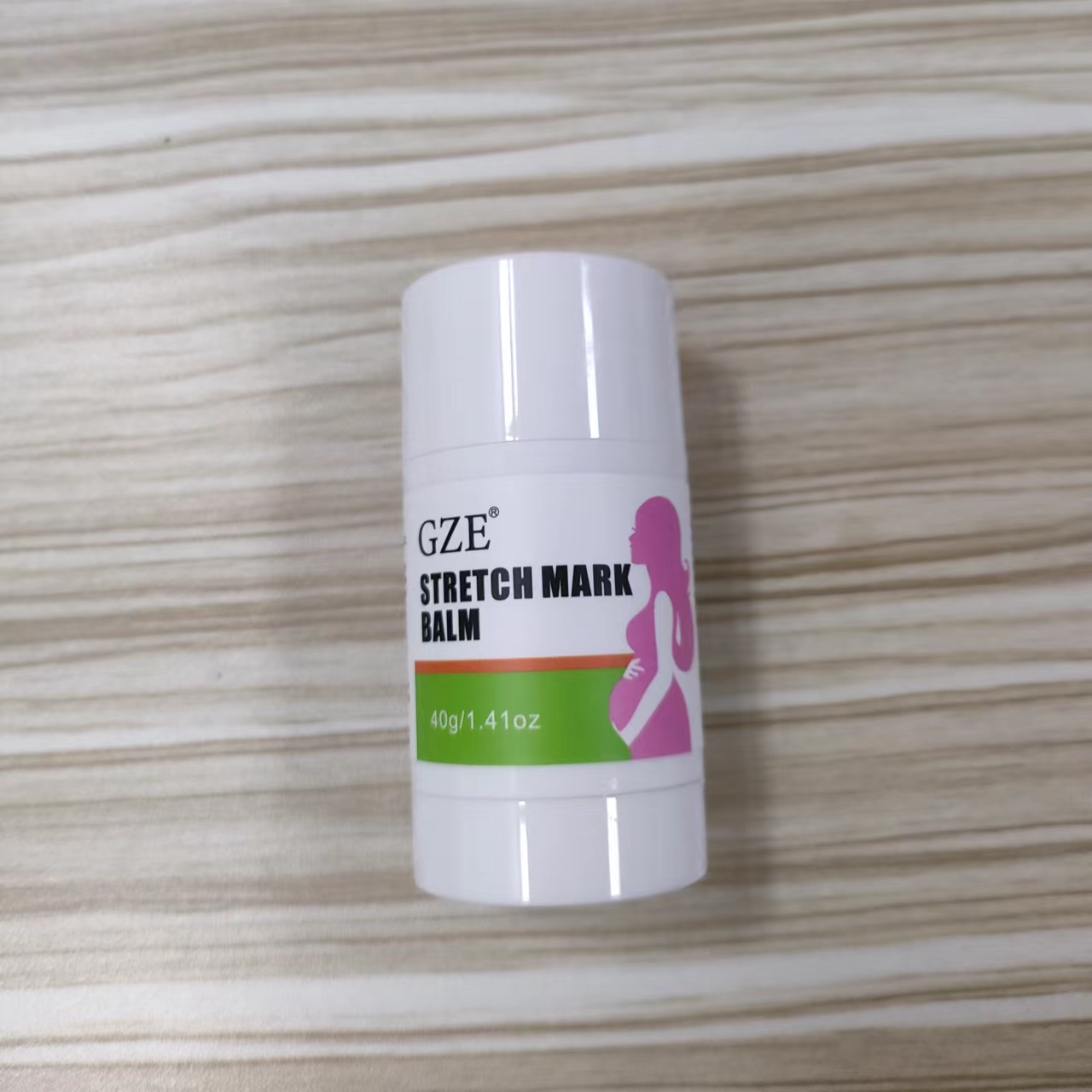 DRUG LABEL: GZE STRETCH MARK BALM
NDC: 74458-271 | Form: STICK
Manufacturer: Guangzhou Yilong Cosmetics Co., Ltd
Category: otc | Type: HUMAN OTC DRUG LABEL
Date: 20241222

ACTIVE INGREDIENTS: APRICOT KERNEL OIL 47.42 g/100 g; BUTYROSPERMUM PARKII (SHEA) BUTTER 12.3 g/100 g
INACTIVE INGREDIENTS: LAVANDULA ANGUSTIFOLIA (LAVENDER) FLOWER; WHITE WAX; CALENDULA OFFICINALIS FLOWER; LAVANDULA ANGUSTIFOLIA (LAVENDER) OIL

GZE STRETCH MARK BALM

ACTIVE INGREDIENT

Prunus Armeniaca (Apricot) Kernel Oil

Butyrospermum Parkii (Shea) Butter

INACTIVE INGREDIENT

Cera Alba

Lavandula Angustifolia (Lavender) Flower Extract

Calendula Officinalis Flower Extract

Lavandula Angustifolia (Lavender) Oil

INDICATIONS AND USAGE

Rub onto growing belly and
breasts to help moisturize and nourish skin

PURPOSE

Moisturizing

WARNINGS

For external use only.

Stop use and ask a doctor if rash occurs.

Do not use on damaged or broken skin

When using this product keep out of eyes. Rinse with water to remove.

Keep out of reach of children. If swallowed, get medical help or contact a Poison Control Center right away.

DOSAGE AND ADMINISTRATION

Rub onto growing belly and
breasts to help moisturize and nourish skin